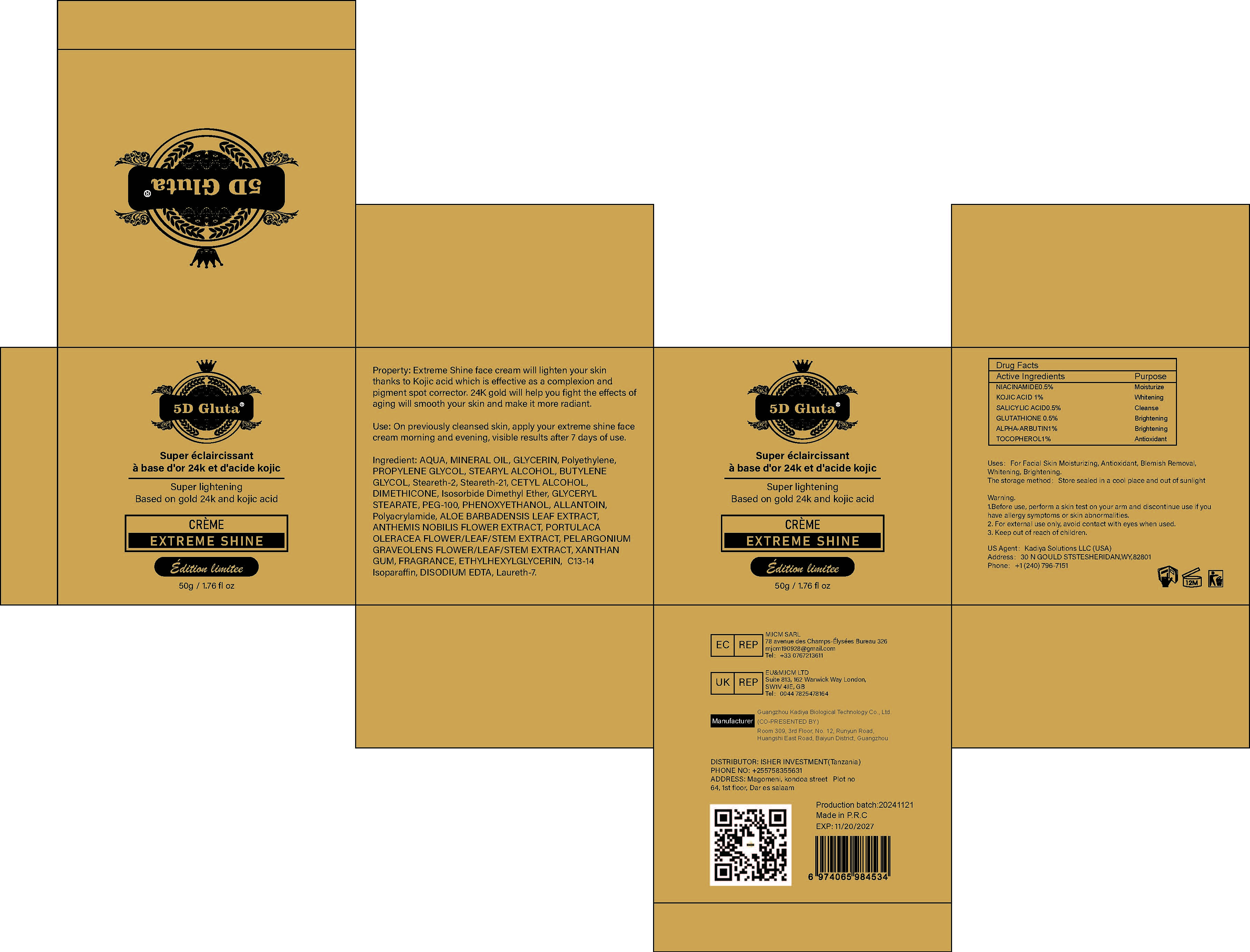 DRUG LABEL: Super Lightening Based on Gold 24k and Kojic Acid Cream
NDC: 84423-068 | Form: CREAM, AUGMENTED
Manufacturer: Guangzhou Kadiya Biotechnology Co., Ltd.
Category: otc | Type: HUMAN OTC DRUG LABEL
Date: 20250217

ACTIVE INGREDIENTS: KOJIC ACID 0.5 g/50 g; GLUTATHIONE 0.25 g/50 g; NIACINAMIDE 0.25 g/50 g; SALICYLIC ACID 0.25 g/50 g; ALPHA-ARBUTIN 0.5 g/50 g; TOCOPHEROL 0.5 g/50 g
INACTIVE INGREDIENTS: AQUA; LAURETH-7; ALOE BARBADENSIS LEAF; PROPYLENE GLYCOL; PHENOXYETHANOL; XANTHAN GUM; ETHYLHEXYLGLYCERIN; GLYCERIN; STEARETH-2; DIMETHICONE; PEG-100; GLYCERYL STEARATE; POLYACRYLAMIDE (10000 MW); ALLANTOIN; DIMETHYL ISOSORBIDE; C13-14 ISOPARAFFIN; STEARYL ALCOHOL; EDETATE DISODIUM; ANTHEMIS NOBILIS FLOWER OIL; PELARGONIUM GRAVEOLENS WHOLE; MINERAL OIL; PORTULACA OLERACEA WHOLE; CETYL ALCOHOL; STEARETH-21; POLYETHYLENE; BUTYLENE GLYCOL

PURPOSE

For Facial Skin Moisturizing, Antioxidant, Blemish Removal, Whitening, Brightening

INACTIVE INGREDIENT

AQUA，MINERAL OIL，GLYCERIN，Polyethylene，PROPYLENE GLYCOL，STEARYL ALCOHOL，BUTYLENE GLYCOL，Steareth-2，Steareth-21，CETYL ALCOHOL，DIMETHICONE，Isosorbide Dimethyl Ether，GLYCERYL STEARATE，PEG-100，PHENOXYETHANOL，ALLANTOIN，Polyacrylamide，ALOE BARBADENSIS LEAF EXTRACT，ANTHEMIS NOBILIS FLOWER EXTRACT，PORTULACA OLERACEA FLOWER/LEAF/STEM EXTRACT，PELARGONIUM GRAVEOLENS FLOWER/LEAF/STEM EXTRACT，XANTHAN GUM，FRAGRANCE，ETHYLHEXYLGLYCERIN， C13-14 Isoparaffin，DISODIUM EDTA，Laureth-7

Warning.
1.Before use, perform a skin test on your arm and discontinue use if you have allergy symptoms or skin abnormalities.
2、For external use only, avoid contact with eyes when used
3、Keep out of reach of children

INACTIVE INGREDIENT

Extreme Shine face cream will lighten your skin thanks to Kojic acid which is effective as a complexion and pigment spot corrector

DOSAGE AND ADMINISTRATION

On previously cleansed skin, apply your extreme shine face cream morning and evening, visible results after 7 days of use.

KEEP OUT OF REACH OF CHILDREN SECTION

Active Ingredients
NIACINAMIDE0.5%
KOJIC ACID 1%
SALICYLIC ACID0.5%
GLUTATHIONE 0.5%
ALPHA-ARBUTIN1%
TOCOPHEROL1%

INDICATIONS AND USAGE

Extreme Shine face cream will lighten your skin thanks to Kojic acid which is effective as a complexion and pigment spot corrector. 24K gold will help you fight the effects of aging will smooth your skin and make it more radiant.

PACKAGE LABEL

NIACINAMIDE0.5%
KOJIC ACID 1%
SALICYLIC ACID0.5%
GLUTATHIONE 0.5%
ALPHA-ARBUTIN1%
TOCOPHEROL1%

Uses：
For Facial Skin Moisturizing, Antioxidant, Blemish Removal, Whitening, Brightening
The storage method：
Store sealed in a cool place and out of sunlight

Warning.
1.Before use, perform a skin test on your arm and discontinue use if you have allergy symptoms or skin abnormalities.
2、For external use only, avoid contact with eyes when used
3、Keep out of reach of children

Inactive ingredients：
AQUA，MINERAL OIL，GLYCERIN，Polyethylene，PROPYLENE GLYCOL，STEARYL ALCOHOL，BUTYLENE GLYCOL，Steareth-2，Steareth-21，CETYL ALCOHOL，DIMETHICONE，Isosorbide Dimethyl Ether，GLYCERYL STEARATE，PEG-100，PHENOXYETHANOL，ALLANTOIN，Polyacrylamide，ALOE BARBADENSIS LEAF EXTRACT，ANTHEMIS NOBILIS FLOWER EXTRACT，PORTULACA OLERACEA FLOWER/LEAF/STEM EXTRACT，PELARGONIUM GRAVEOLENS FLOWER/LEAF/STEM EXTRACT，XANTHAN GUM，FRAGRANCE，ETHYLHEXYLGLYCERIN， C13-14 Isoparaffin，DISODIUM EDTA，Laureth-7